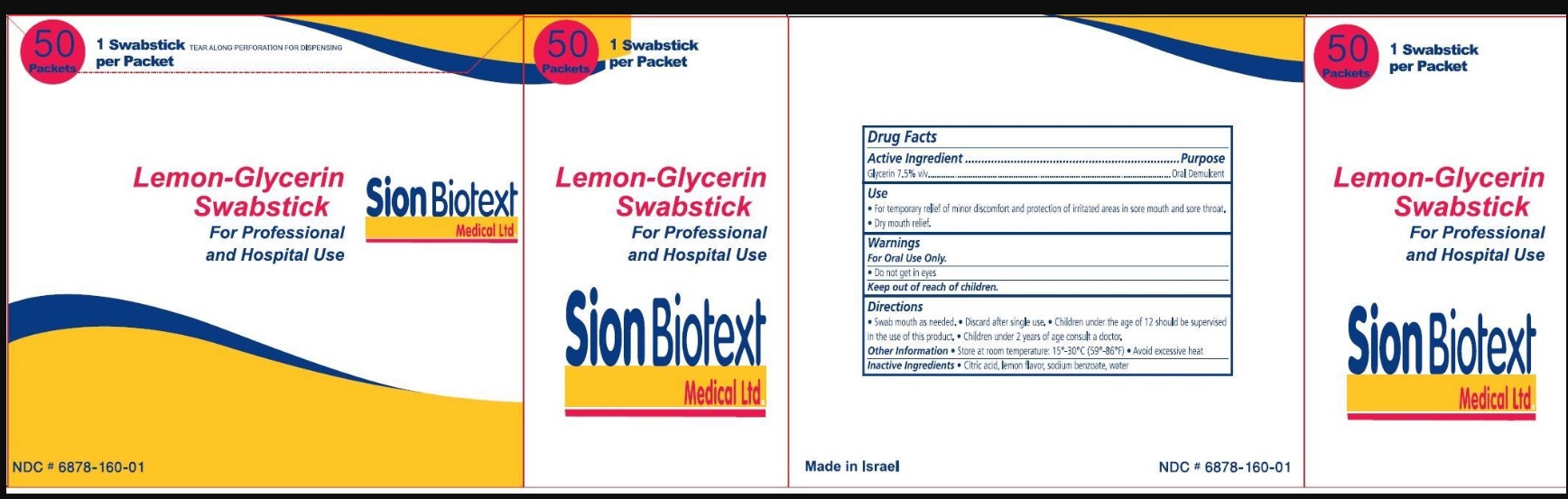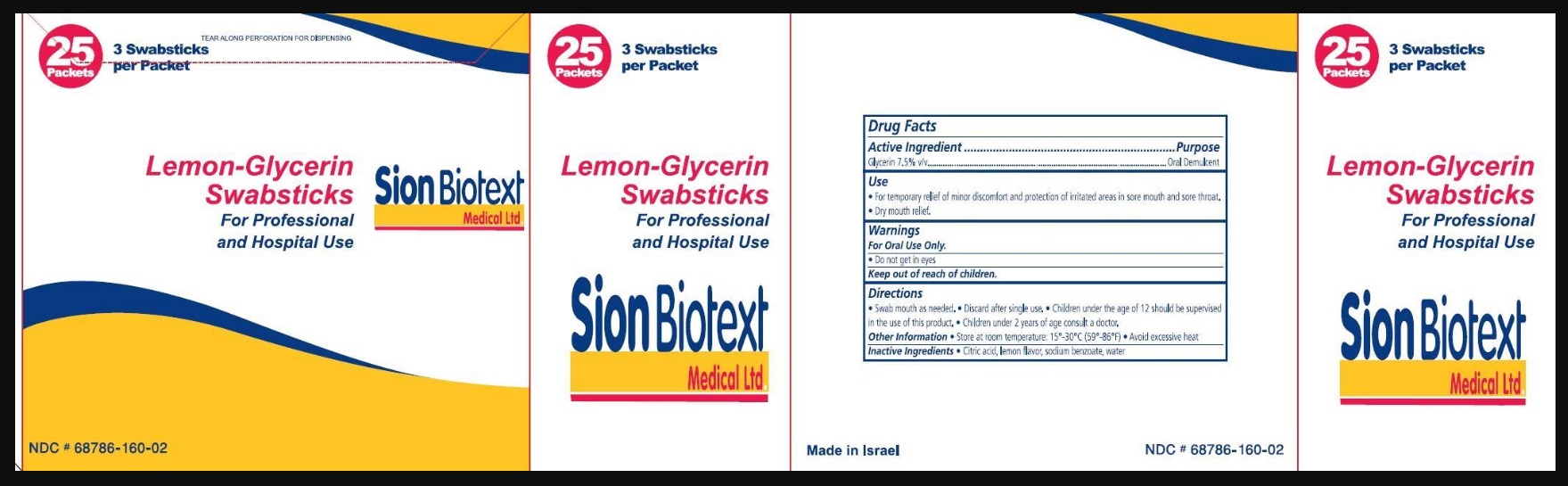 DRUG LABEL: Lemon
NDC: 68786-160 | Form: SWAB
Manufacturer: Sion Biotext Medical Ltd
Category: otc | Type: HUMAN OTC DRUG LABEL
Date: 20240410

ACTIVE INGREDIENTS: GLYCERIN 7.5 mg/100 mg
INACTIVE INGREDIENTS: SODIUM BENZOATE; CITRIC ACID MONOHYDRATE; WATER

Lemon Glycerin Swabsticks

Active Ingredient

Glycerin 7.5% v/v

Purpose

Oral Demulcent

Warning:

For Oral Use Only.

- Do not get in eyes.

Keep out of reach of children.

Use

- For temporary relief of minor discomfort and protection of irritated areas in sore mouth and sore throat.
- Dry mouth relief.

Directions

- Swab mouth as needed.
- Discard after single use.
- Children under the age of 12 should be supervised in the use of this product.
- Children under 2 years of age consult a doctor.

Other information

- Store at room temperature. 15° C- 30°C (59°F - 86°F)
- Avoid excessive heat.

Inactive ingredients

Citric acid, lemon flavor, sodium benzoate, water

Principle Display Panel

25 packets

3 swabsticks per packet

Lemon-Glycerin Swabstick

For Professional and Hospital Use

Sion Biotext Medical Ltd

68786-160-02

50 packets

1 swabstick per packet

Lemon-Glycerin Swabstick

For Professional and Hospital Use

Sion Biotext Medical Ltd

68786-160-01